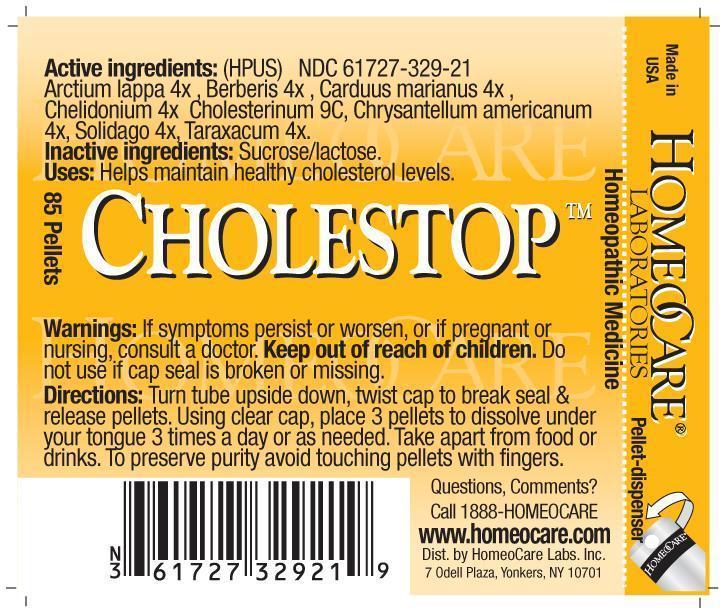 DRUG LABEL: Cholestop
NDC: 61727-329 | Form: PELLET
Manufacturer: Homeocare Laboratories
Category: homeopathic | Type: HUMAN OTC DRUG LABEL
Date: 20210113

ACTIVE INGREDIENTS: ARCTIUM LAPPA WHOLE 4 [hp_X]/4 g; BERBERIS VULGARIS ROOT BARK 4 [hp_X]/4 g; SILYBUM MARIANUM SEED 4 [hp_X]/4 g; CHELIDONIUM MAJUS 4 [hp_X]/4 g; CHOLESTEROL 9 [hp_C]/4 g; CHRYSANTHELLUM INDICUM SUBSP. AFROAMERICANUM 4 [hp_X]/4 g; SOLIDAGO CANADENSIS FLOWERING TOP 4 [hp_X]/4 g; TARAXACUM PALUSTRE ROOT 4 [hp_X]/4 g
INACTIVE INGREDIENTS: SUCROSE; LACTOSE

Cholestop

Active Ingredients:

Arctium lappa 4X, Berberis 4X, Carduus marianus 4X, Chelidonium 4X, Cholesterinum 9C, Chrysantellum americanum 4x, Solidago 4X, Taraxacum 4X.

Inactive Ingredients:

Sucrose/lactose.

Purpose:

Helps maintain healthy cholesterol levels.

Keep out of reach of children.

Indications & Usage:

Turn tube upside down, twist cap to break seal & release pellets. Using clear cap, place 3 pellets to dissolve under your tongue 3 times a day or as needed. Take apart from food or drinks. To preserve purity avoid touching pellets with fingers.

Dosage & Administration:

Turn tube upside down, twist cap to break seal & release pellets. Using clear cap, place 3 pellets to dissolve under your tongue 3 times a day or as needed. Take apart from food or drinks. To preserve purity avoid touching pellets with fingers.

Warnings:

If symptoms persist or worsen, or if pregnant or nursing, consult a doctor. Keep out of reach of children. Do not use if cap seal is broken or mssing.

Cholestop

Homeopathic Medicine

85 Pellets

hcl_label_cholestop-2012.jpg